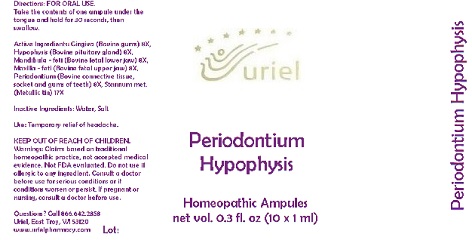 DRUG LABEL: Periodontium Hypophysis
NDC: 48951-8016 | Form: LIQUID
Manufacturer: Uriel Pharmacy Inc.
Category: homeopathic | Type: HUMAN OTC DRUG LABEL
Date: 20180525

ACTIVE INGREDIENTS: BEEF TONGUE 8 [hp_X]/1 mL; BOS TAURUS PITUITARY GLAND 8 [hp_X]/1 mL; BOS TAURUS BONE 8 [hp_X]/1 mL; SUS SCROFA TOOTH 8 [hp_X]/1 mL; TIN 17 [hp_X]/1 mL
INACTIVE INGREDIENTS: WATER; SODIUM CHLORIDE

Periodontium Hypophysis

INDICATIONS AND USAGE

Directions: FOR ORAL USE ONLY.

DOSAGE AND ADMINISTRATION

Take the contents of one ampule under the tongue and hold for 30 seconds, then swallow.

ACTIVE INGREDIENT

Active Ingredients: Gingiva (Bovine gums) 8X, Hypophysis (Bovine pituitary gland) 8X, Mandibula - feti (Bovine fetal lower jaw) 8X, Maxilla - feti (Bovine fetal upper jaw) 8X, Periodontium (Bovine connective tissue, socket and gums of teeth) 8X, Stannum met. (Metallic tin) 17X

Inactive Ingredients: Water, Salt

PURPOSE

Use: Temporary relief of headache.

KEEP OUT OF REACH OF CHILDREN.

WARNINGS

Warnings: Claims based on traditional homeopathic practice, not accepted medical evidence. Not FDA evaluated. Do not use if allergic to any ingredient. Consult a doctor before use for serious conditions or if conditions worsen or persist. If pregnant or nursing, consult a doctor before use.

QUESTIONS

Questions? Call 866.642.2858 Uriel, East Troy, WI 53120 www.urielpharmacy.com